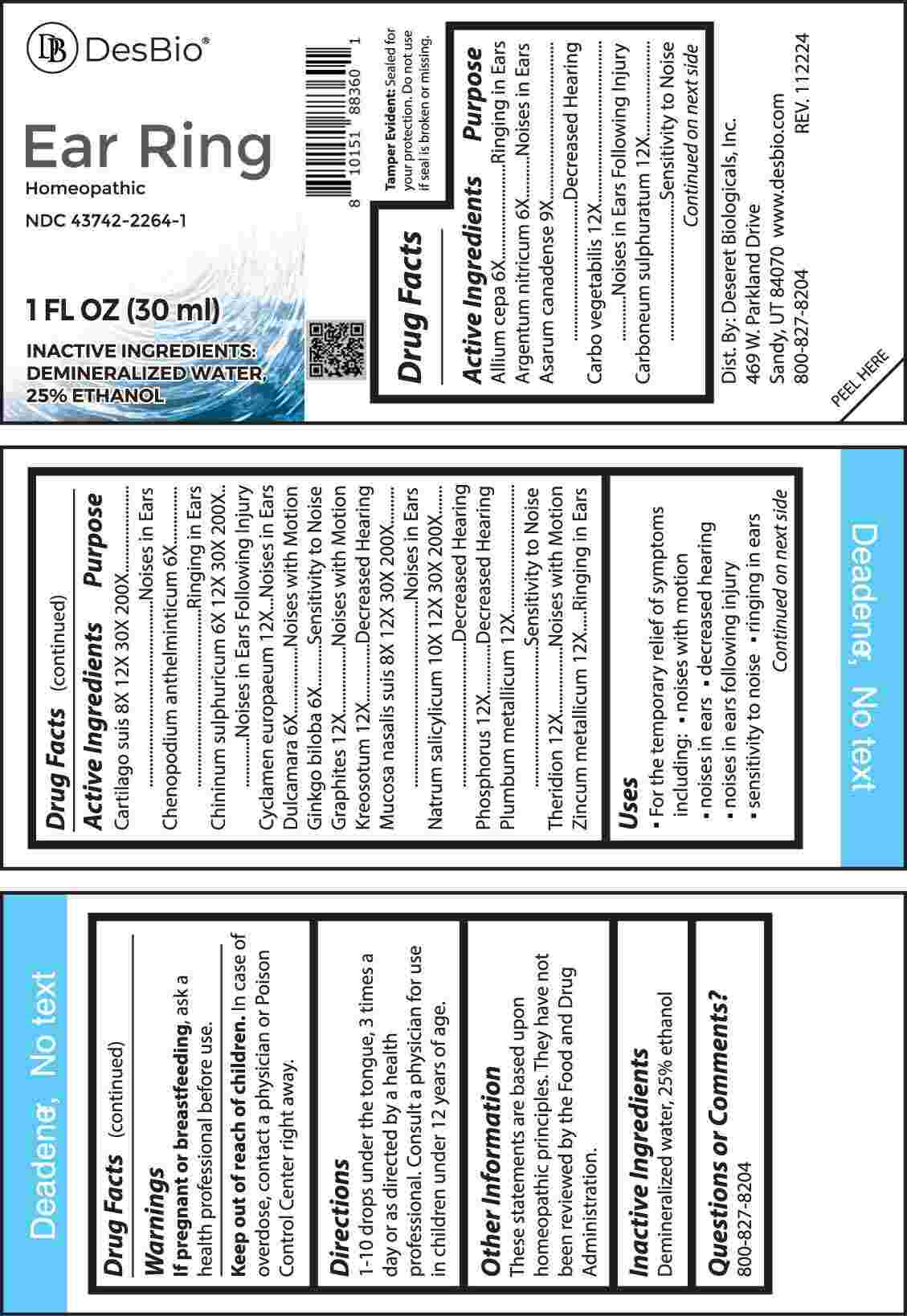 DRUG LABEL: Ear Ring
NDC: 43742-2264 | Form: LIQUID
Manufacturer: Deseret Biologicals, Inc.
Category: homeopathic | Type: HUMAN OTC DRUG LABEL
Date: 20250429

ACTIVE INGREDIENTS: ONION 6 [hp_X]/1 mL; SILVER NITRATE 6 [hp_X]/1 mL; ASARUM CANADENSE ROOT 9 [hp_X]/1 mL; ACTIVATED CHARCOAL 12 [hp_X]/1 mL; CARBON DISULFIDE 12 [hp_X]/1 mL; SUS SCROFA CARTILAGE 8 [hp_X]/1 mL; DYSPHANIA AMBROSIOIDES WHOLE 6 [hp_X]/1 mL; QUININE SULFATE 6 [hp_X]/1 mL; CYCLAMEN PURPURASCENS TUBER 12 [hp_X]/1 mL; SOLANUM DULCAMARA TOP 6 [hp_X]/1 mL; GINKGO 6 [hp_X]/1 mL; GRAPHITE 12 [hp_X]/1 mL; WOOD CREOSOTE 12 [hp_X]/1 mL; SUS SCROFA NASAL MUCOSA 8 [hp_X]/1 mL; SODIUM SALICYLATE 10 [hp_X]/1 mL; PHOSPHORUS 12 [hp_X]/1 mL; LEAD 12 [hp_X]/1 mL; THERIDION CURASSAVICUM 12 [hp_X]/1 mL; ZINC 12 [hp_X]/1 mL
INACTIVE INGREDIENTS: WATER; ALCOHOL

DRUG FACTS:

ACTIVE INGREDIENTS:

Allium Cepa 6X, Argentum Nitricum 6X, Asarum Canadense 9X, Carbo Vegetabilis 12X, Carboneum Sulphuratum 12X, Cartilago Suis 8X, 12X, 30X, 200X, Chenopodium Anthelminticum 6X, Chininum Sulphuricum 6X, Cyclamen Europaeum 12X, Dulcamara 6X, Ginkgo Biloba 6X, Graphites 12X, Kreosotum 12X, Mucosa Nasalis Suis 8X, 12X, 30X, 200X, Natrum Salicylicum 10X 12X, 30X, 200X, Phosphorus 12X, Plumbum Metallicum 12X, Theridion 12X, Zincum Metallicum 12X.

PURPOSE:

Allium Cepa – Ringing in Ears, Argentum Nitricum – Noise in Ears, Asarum Canadense – Decreased Hearing, Carbo Vegetabilis – Noises in Ears Following Injury, Carboneum Sulphuratum – Sensitivity to Noise, Cartilago Suis – Noises in Ears, Chenopodium Anthelminticum – Ringing in Ears, Chininum Sulphuricum – Noises in Ears Following Injury, Cyclamen Europaeum – Noises in Ears, Dulcamara – Noises with Motion, Ginkgo Biloba – Sensitivity to Noise, Graphites – Noises with Motion, Kreosotum – Decreased Hearing, Mucosa Nasalis Suis – Noises in Ears, Natrum Salicylicum - Decreased Hearing, Phosphorus – Decreased Hearing, Plumbum Metallicum – Sensitivity to Noise, Theridion – Noises with Motion, Zincum Metallicum – Ringing in Ears

USES:

• For the temporary relief of symptoms including:

• noises with motion • noises in ears • decreased hearing

• noises in ears following injury • sensitivity to noise • ringing in ears

These statements are based upon homeopathic principles. They have not been reviewed by the Food and Drug Administration.

WARNINGS:

If pregnant or breastfeeding, ask a health professional before use.

Keep out of reach of children. In case of overdose, contact a physician or Poison Control Center right away.

Tamper Evident: Sealed for your protection. Do not use if seal is broken or missing.

KEEP OUT OF REACH OF CHILDREN:

In case of overdose, contact a physician or Poison Control Center right away.

DIRECTIONS:

1-10 drops under the tongue, 3 times a day or as directed by a health professional. Consult a physician for use in children under 12 years of age.

INACTIVE INGREDIENTS:

Demineralized water, 25% ethanol

QUESTIONS:

Dist. By: Deseret Biologicals, Inc.

469 W. Parkland Drive

Sandy, UT 84070

www.desbio.com'

800-827-8204

PACKAGE LABEL DISPLAY:

DesBio

Ear Ring

Homeopathic

NDC 43742-2264-1

1 FL OZ (30 ml)